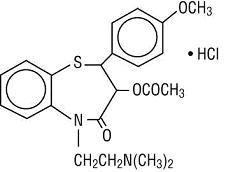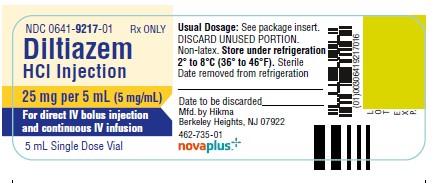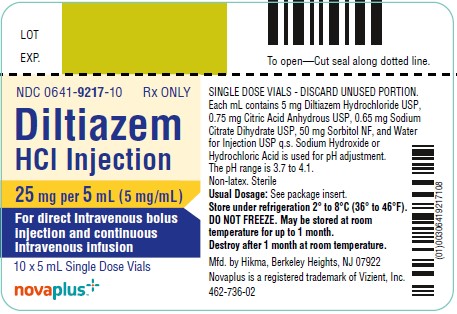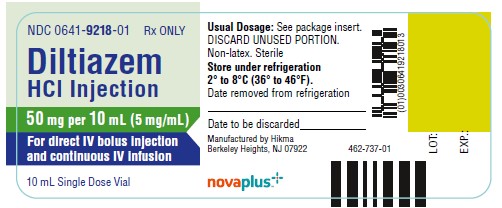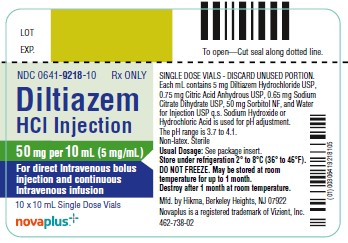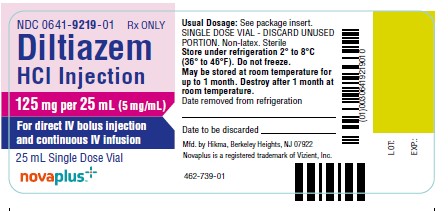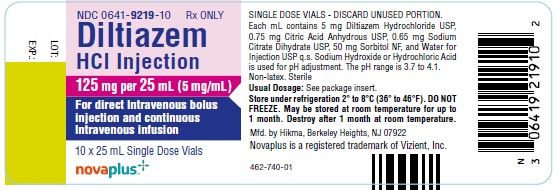 DRUG LABEL: Diltiazem Hydrochloride
NDC: 0641-9217 | Form: INJECTION
Manufacturer: Hikma Pharmaceuticals USA Inc.
Category: prescription | Type: HUMAN PRESCRIPTION DRUG LABEL
Date: 20260209

ACTIVE INGREDIENTS: DILTIAZEM HYDROCHLORIDE 5 mg/1 mL
INACTIVE INGREDIENTS: ANHYDROUS CITRIC ACID 0.75 mg/1 mL; SODIUM CITRATE 0.65 mg/1 mL; SORBITOL 50 mg/1 mL; WATER; SODIUM HYDROXIDE; HYDROCHLORIC ACID

Diltiazem Hydrochloride Injection
Rx Only NOVAPLUS®

DESCRIPTION

Diltiazem hydrochloride is a calcium ion influx inhibitor (slow channel blocker or calcium channel antagonist). Chemically, diltiazem hydrochloride is (+)-5-[2-(Dimethylamino)ethyl]-cis-2,3-dihydro-3-hydroxy-2-(p-methoxyphenyl)-1,5-benzothiazepin-4(5H)-one acetate(ester) monohydrochloride. The structural formula is:

C22H26N2O4S• HCl MW: 450.98

Diltiazem hydrochloride is a white to off-white crystalline powder with a bitter taste. It is soluble in water, methanol, and chloroform.

Diltiazem hydrochloride injection is a clear, colorless, sterile, nonpyrogenic solution. It has a pH range of 3.7 to 4.1.

Diltiazem hydrochloride injection is for direct intravenous bolus injection and continuous intravenous infusion.

Each mL contains: 5 mg Diltiazem Hydrochloride, USP, 0.75 mg Citric Acid Anhydrous, USP, 0.65 mg Sodium Citrate Dihydrate USP, 50 mg Sorbitol NF, and Water for Injection, USP q.s. Sodium Hydroxide or Hydrochloric Acid is used to adjust pH.

CLINICAL PHARMACOLOGY

Mechanisms of Action

Diltiazem inhibits the influx of calcium (Ca ^2+) ions during membrane depolarization of cardiac and vascular smooth muscle. The therapeutic benefits of diltiazem in supraventricular tachycardias are related to its ability to slow AV nodal conduction time and prolong AV nodal refractoriness. Diltiazem exhibits frequency (use) dependent effects on AV nodal conduction such that it may selectively reduce the heart rate during tachycardias involving the AV node with little or no effect on normal AV nodal conduction at normal heart rates.

Diltiazem slows the ventricular rate in patients with a rapid ventricular response during atrial fibrillation or atrial flutter. Diltiazem converts paroxysmal supraventricular tachycardia (PSVT) to normal sinus rhythm by interrupting the reentry circuit in AV nodal reentrant tachycardias and reciprocating tachycardias, e.g., Wolff-Parkinson-White syndrome (WPW).

Diltiazem prolongs the sinus cycle length. It has no effect on the sinus node recovery time or on the sinoatrial conduction time in patients without SA nodal dysfunction. Diltiazem has no significant electrophysiologic effects on tissues in the heart that are fast sodium channel dependent, e.g., His-Purkinje tissue, atrial and ventricular muscle, and extranodal accessory pathways.

Like other calcium channel antagonists, because of its effect on vascular smooth muscle, diltiazem decreases total peripheral resistance resulting in a decrease in both systolic and diastolic blood pressure.

Hemodynamics

In patients with cardiovascular disease, diltiazem hydrochloride administered intravenously in single bolus doses, followed in some cases by a continuous infusion, reduced blood pressure, systemic vascular resistance, the rate-pressure product, and coronary vascular resistance and increased coronary blood flow. In a limited number of studies of patients with compromised myocardium (severe congestive heart failure, acute myocardial infarction, hypertrophic cardiomyopathy), administration of intravenous diltiazem produced no significant effect on contractility, left ventricular end diastolic pressure, or pulmonary capillary wedge pressure. The mean ejection fraction and cardiac output/index remained unchanged or increased. Maximal hemodynamic effects usually occurred within 2 to 5 minutes of an injection. However, in rare instances, worsening of congestive heart failure has been reported in patients with preexisting impaired ventricular function.

Pharmacodynamics

The prolongation of PR interval correlated significantly with plasma diltiazem concentration in normal volunteers using the Sigmoidal Emax model. Changes in heart rate, systolic blood pressure, and diastolic blood pressure did not correlate with diltiazem plasma concentrations in normal volunteers. Reduction in mean arterial pressure correlated linearly with diltiazem plasma concentration in a group of hypertensive patients.

In patients with atrial fibrillation and atrial flutter, a significant correlation was observed between the percent reduction in HR and plasma diltiazem concentration using the Sigmoidal Emax model. Based on this relationship, the mean plasma diltiazem concentration required to produce a 20% decrease in heart rate was determined to be 80 ng/mL. Mean plasma diltiazem concentrations of 130 ng/mL and 300 ng/mL were determined to produce reductions in heart rate of 30% and 40%.

Pharmacokinetics and Metabolism

Following a single intravenous injection in healthy male volunteers, diltiazem hydrochloride appears to obey linear pharmacokinetics over a dose range of 10.5 to 21 mg. The plasma elimination half-life is approximately 3.4 hours. The apparent volume of distribution of diltiazem is approximately 305 L. Diltiazem is extensively metabolized in the liver with a systemic clearance of approximately 65 L/h.

After constant rate intravenous infusion to healthy male volunteers, diltiazem exhibits nonlinear pharmacokinetics over an infusion range of 4.8 to 13.2 mg/h for 24 hours. Over this infusion range, as the dose is increased, systemic clearance decreases from 64 to 48 L/h while the plasma elimination half-life increases from 4.1 to 4.9 hours. The apparent volume of distribution remains unchanged (360 to 391 L). In patients with atrial fibrillation or atrial flutter, diltiazem systemic clearance has been found to be decreased compared to healthy volunteers. In patients administered bolus doses ranging from 2.5 mg to 38.5 mg, systemic clearance averaged 36 L/h. In patients administered continuous infusions at 10 mg/h or 15 mg/h for 24 hours, diltiazem systemic clearance averaged 42 L/h and 31 L/h, respectively.

Based on the results of pharmacokinetic studies in healthy volunteers administered different oral diltiazem hydrochloride formulations, constant rate intravenous infusions of diltiazem hydrochloride at 3, 5, 7, and 11 mg/h are predicted to produce steady-state plasma diltiazem concentrations equivalent to 120-, 180-, 240-, and 360-mg total daily oral doses of diltiazem hydrochloride tablets or diltiazem hydrochloride extended-release capsules.

After oral administration, diltiazem undergoes extensive metabolism in man by deacetylation, N-demethylation, and O-demethylation via cytochrome P-450 (oxidative metabolism) in addition to conjugation. Metabolites N-monodesmethyldiltiazem, desacetyldiltiazem, desacetyl-N-monodesmethyldiltiazem, desacetyl-O-desmethyldiltiazem, and desacetyl-N, O-desmethyldiltiazem have been identified in human urine. Following oral administration, 2% to 4% of the unchanged diltiazem appears in the urine. Drugs which induce or inhibit hepatic microsomal enzymes may alter diltiazem disposition.

Following single intravenous injection of diltiazem hydrochloride, however, plasma concentrations of N-mono-desmethyldiltiazem and desacetyldiltiazem, two principal metabolites found in plasma after oral administration, are typically not detected. These metabolites are observed, however, following 24 hour constant rate intravenous infusion. Total radioactivity measurement following short IV administration in healthy volunteers suggests the presence of other unidentified metabolites which attain higher concentrations than those of diltiazem and are more slowly eliminated; half-life of total radioactivity is about 20 hours compared to 2 to 5 hours for diltiazem.

Diltiazem hydrochloride is 70% to 80% bound to plasma proteins. In vitro studies suggest alpha1-acid glycoprotein binds approximately 40% of the drug at clinically significant concentrations. Albumin appears to bind approximately 30% of the drug, while other constituents bind the remaining bound fraction. Competitive in vitro ligand binding studies have shown that diltiazem hydrochloride binding is not altered by therapeutic concentrations of digoxin, phenytoin, hydrochlorothiazide, indomethacin, phenylbutazone, propranolol, salicylic acid, tolbutamide, or warfarin.

Renal insufficiency, or even end-stage renal disease, does not appear to influence diltiazem disposition following oral administration. Liver cirrhosis was shown to reduce diltiazem’s apparent oral clearance and prolong its half-life.

INDICATIONS AND USAGE

Diltiazem Hydrochloride Injection is indicated for the following:

Atrial Fibrillation or Atrial Flutter

Temporary control of rapid ventricular rate in atrial fibrillation or atrial flutter. It should not be used in patients with atrial fibrillation or atrial flutter associated with an accessory bypass tract such as in Wolff-Parkinson-White (WPW) syndrome or short PR syndrome.

Paroxysmal Supraventricular Tachycardia

Rapid conversion of paroxysmal supraventricular tachycardias (PSVT) to sinus rhythm. This includes AV nodal reentrant tachycardias and reciprocating tachycardias associated with an extranodal accessory pathway such as the WPW syndrome or short PR syndrome. Unless otherwise contraindicated, appropriate vagal maneuvers should be attempted prior to administration of diltiazem hydrochloride injection.

The use of diltiazem hydrochloride injection should be undertaken with caution when the patient is compromised hemodynamically or is taking other drugs that decrease any or all of the following: peripheral resistance, myocardial filling, myocardial contractility, or electrical impulse propagation in the myocardium.

For either indication and particularly when employing continuous intravenous infusion, the setting should include continuous monitoring of the ECG and frequent measurement of blood pressure. A defibrillator and emergency equipment should be readily available.

In domestic controlled trials in patients with atrial fibrillation or atrial flutter, bolus administration of diltiazem hydrochloride injection was effective in reducing heart rate by at least 20% in 95% of patients. Diltiazem hydrochloride injection rarely converts atrial fibrillation or atrial flutter to normal sinus rhythm. Following administration of one or two intravenous bolus doses of diltiazem injection, response usually occurs within 3 minutes and maximal heart rate reduction generally occurs in 2 to 7 minutes. Heart rate reduction may last from 1 to 3 hours. If hypotension occurs, it is generally short-lived, but may last from 1 to 3 hours.

A 24-hour continuous infusion of diltiazem injection in the treatment of atrial fibrillation or atrial flutter maintained at least a 20% heart rate reduction during the infusion in 83% of patients. Upon discontinuation of infusion, heart rate reduction may last from 0.5 hours to more than 10 hours (median duration 7 hours). Hypotension, if it occurs, may be similarly persistent.

In the controlled clinical trials, 3.2% of patients required some form of intervention (typically, use of intravenous fluids or the Trendelenburg position) for blood pressure support following diltiazem hydrochloride injection.

In domestic controlled trials, bolus administration of diltiazem hydrochloride injection was effective in converting PSVT to normal sinus rhythm in 88% of patients within 3 minutes of the first or second bolus dose.

Symptoms associated with the arrhythmia were improved in conjunction with decreased heart rate or conversion to normal sinus rhythm following administration of diltiazem hydrochloride injection.

CONTRAINDICATIONS

Diltiazem hydrochloride injection is contraindicated in:

1. Patients with sick sinus syndrome except in the presence of a functioning ventricular pacemaker.
2. Patients with second- or third-degree AV block except in the presence of a functioning ventricular pacemaker.
3. Patients with severe hypotension or cardiogenic shock.
4. Patients who have demonstrated hypersensitivity to the drug.
5. Intravenous diltiazem and intravenous beta-blockers should not be administered together or in close proximity (within a few hours).
6. Patients with atrial fibrillation or atrial flutter associated with an accessory bypass tract such as in WPW syndrome or short PR syndrome. As with other agents which slow AV nodal conduction and do not prolong the refractoriness of the accessory pathway (e.g., verapamil, digoxin), in rare instances patients in atrial fibrillation or atrial flutter associated with an accessory bypass tract may experience a potentially life-threatening increase in heart rate accompanied by hypotension when treated with diltiazem hydrochloride injection. As such, the initial use of diltiazem hydrochloride injection should be, if possible, in a setting where monitoring and resuscitation capabilities, including DC cardioversion/defibrillation, are present (see OVERDOSAGE). Once familiarity of the patient’s response is established, use in an office setting may be acceptable.
7. Patients with ventricular tachycardia. Administration of other calcium channel blockers to patients with wide complex tachycardia (QRS ≥0.12 seconds) has resulted in hemodynamic deterioration and ventricular fibrillation. It is important that an accurate pretreatment diagnosis distinguish wide complex QRS tachycardia of superventricular origin from that of ventricular origin prior to administration of diltiazem hydrochloride injection.

WARNINGS

Cardiac Conduction

Diltiazem prolongs AV nodal conduction and refractoriness that may rarely result in second- or third-degree AV block in sinus rhythm. Concomitant use of diltiazem with agents known to affect cardiac conduction may result in additive effects (see PRECAUTIONS, Drug Interactions). If high-degree AV block occurs in sinus rhythm, intravenous diltiazem should be discontinued and appropriate supportive measures instituted (see OVERDOSAGE).

Congestive Heart Failure

Although diltiazem has a negative inotropic effect in isolated animal tissue preparations, hemodynamic studies in humans with normal ventricular function and in patients with a compromised myocardium, such as severe CHF, acute MI, and hypertrophic cardiomyopathy, have not shown a reduction in cardiac index nor consistent negative effects on contractility (dp/dt). Administration of oral diltiazem in patients with acute myocardial infarction and pulmonary congestion documented by x-ray on admission is contraindicated. Experience with the use of diltiazem hydrochloride injection in patients with impaired ventricular function is limited. Caution should be exercised when using the drug in such patients.

Hypotension

Decreases in blood pressure associated with diltiazem hydrochloride injection therapy may occasionally result in symptomatic hypotension (3.2%). The use of intravenous diltiazem for control of ventricular response in patients with supraventricular arrhythmias should be undertaken with caution when the patient is compromised hemodynamically. In addition, caution should be used in patients taking other drugs that decrease peripheral resistance, intravascular volume, myocardial contractility or conduction.

Acute Hepatic Injury

In rare instances, significant elevations in enzymes such as alkaline phosphatase, LDH, SGOT, SGPT, and other phenomena consistent with acute hepatic injury have been noted following oral diltiazem. Therefore, the potential for acute hepatic injury exists following administration of intravenous diltiazem.

Ventricular Premature Beats (VPBs)

VPBs may be present on conversion of PSVT to sinus rhythm with diltiazem hydrochloride injection. These VPBs are transient, are typically considered to be benign, and appear to have no clinical significance. Similar ventricular complexes have been noted during cardioversion, other pharmacologic therapy, and during spontaneous conversion of PSVT to sinus rhythm.

PRECAUTIONS

General

Diltiazem hydrochloride is extensively metabolized by the liver and excreted by the kidneys and in bile. The drug should be used with caution in patients with impaired renal or hepatic function (see WARNINGS). High intravenous dosages (4.5 mg/kg tid) administered to dogs resulted in significant bradycardia and alterations in AV conduction. In subacute and chronic dog and rat studies designed to produce toxicity, high oral doses of diltiazem were associated with hepatic damage. In special subacute hepatic studies, oral doses of 125 mg/kg and higher in rats were associated with histological changes in the liver, which were reversible when the drug was discontinued. In dogs, oral doses of 20 mg/kg were also associated with hepatic changes; however, these changes were reversible with continued dosing.

Dermatologic events progressing to erythema multiforme and/or exfoliative dermatitis have been infrequently reported following oral diltiazem. Therefore, the potential for these dermatologic reactions exists following exposure to intravenous diltiazem. Should a dermatologic reaction persist, the drug should be discontinued.

Drug Interactions

As with all drugs, care should be exercised when treating patients with multiple medications. Diltiazem is both a substrate and an inhibitor of the cytochrome P-450 3A4 enzyme system. Other drugs that are specific substrates, inhibitors, or inducers of this enzyme system may have a significant impact on the efficacy and side effect profile of diltiazem. Patients taking other drugs that are substrates of CYP450 3A4, especially patients with renal and/or hepatic impairment, may require dosage adjustment when starting or stopping concomitantly administered diltiazem in order to maintain optimum therapeutic blood levels.

ANESTHETICS

The depression of cardiac contractility, conductivity, and automaticity as well as the vascular dilation associated with anesthetics may be potentiated by calcium channel blockers. When used concomitantly, anesthetics and calcium blockers should be titrated carefully.

BENZODIAZEPINES

Studies showed that diltiazem increased the AUC of midazolam and triazolam by 3-4 fold and Cmaxby 2-fold, compared to placebo. The elimination half-life of midazolam and triazolam also increased (1.5 to 2.5 fold) during coadministration with diltiazem. These pharmacokinectic effects seen during diltiazem coadministration can result in increased clinical effects (e.g. prolonged sedation) of both midazolam and triazolam.

BETA-BLOCKERS

Intravenous diltiazem has been administered to patients on chronic oral beta-blocker therapy. The combination of the two drugs was generally well tolerated without serious adverse effects. If intravenous diltiazem is administered to patients receiving chronic oral beta-blocker therapy, the possibility for bradycardia, AV block, and/or depression of contractility should be considered (see CONTRAINDICATIONS). Oral administration of diltiazem with propranolol in five normal volunteers resulted in increased propranolol levels in all subjects and bioavailability of propranolol was increased approximately 50%. In vitro, propranolol appears to be displaced from its binding sites by diltiazem.

BUSPIRONE

In nine healthy subjects, diltiazem significantly increased the mean buspirone AUC 5.5 fold and Cmax 4.1 fold compared to placebo. The T1/2 and Tmax of buspirone were not significantly affected by diltiazem. Enhanced effects and increased toxicity of buspirone may be possible during concomitant administration with diltiazem. Subsequent dose adjustments may be necessary during coadministration, and should be based on clinical assessment.

CARBAMAZEPINE

Concomitant administration of oral diltiazem with carbamazepine has been reported to result in elevated plasma levels of carbamazepine (by 40 to 72%), resulting in toxicity in some cases. Patients receiving these drugs concurrently should be monitored for a potential drug interaction.

CIMETIDINE

A study in six healthy volunteers has shown a significant increase in peak diltiazem plasma levels (58%) and area-under-the-curve (53%) after a 1-week course of cimetidine at 1200 mg per day and a single dose of diltiazem 60 mg. Ranitidine produced smaller, nonsignificant increases. The effect may be mediated by cimetidine’s known inhibition of hepatic cytochrome P-450, the enzyme system responsible for the first-pass metabolism of diltiazem. Patients currently receiving diltiazem therapy should be carefully monitored for a change in pharmacological effect when initiating and discontinuing therapy with cimetidine. An adjustment in the diltiazem dose may be warranted.

CYCLOSPORINE

A pharmacokinetic interaction between diltiazem and cyclosporine has been observed during studies involving renal and cardiac transplant patients. In renal and cardiac transplant recipients, a reduction of cyclosporine dose ranging from 15% to 48% was necessary to maintain cyclosporine trough concentrations similar to those seen prior to the addition of diltiazem. If these agents are to be administered concurrently, cyclosporine concentrations should be monitored, especially when diltiazem therapy is initiated, adjusted or discontinued.

The effect of cyclosporine on diltiazem plasma concentrations has not been evaluated.

DIGITALIS

Intravenous diltiazem has been administered to patients receiving either intravenous or oral digitalis therapy. The combination of the two drugs was well tolerated without serious adverse effects. However, since both drugs affect AV nodal conduction, patients should be monitored for excessive slowing of the heart rate and/or AV block.

LOVASTATIN

In a ten-subject study, coadministration of diltiazem (120 mg bid, diltiazem SR) with lovastatin resulted in a 3 to 4 times increase in mean lovastatin AUC and Cmax versus lovastatin alone; no change in pravastatin AUC and Cmax was observed during diltiazem coadministration. Diltiazem plasma levels were not significantly affected by lovastatin or pravastatin.

QUINIDINE

Diltiazem significantly increases the AUC(0-∞) of quinidine by 51%, T1/2 by 36% and decreases its CLoral, by 33%. Monitoring for quinidine adverse effects may be warranted and the dose adjusted accordingly.

RIFAMPIN

Coadministration of rifampin with diltiazem lowered the diltiazem plasma concentrations to undetectable levels. Coadministration of diltiazem with rifampin or any known CYP3A4 inducer should be avoided when possible, and alternative therapy considered.

Carcinogenesis, Mutagenesis, Impairment of Fertility

A 24-month study in rats at oral dosage levels of up to 100 mg/kg/day, and a 21- month study in mice at oral dosage levels of up to 30 mg/kg/day showed no evidence of carcinogenicity. There was also no mutagenic response in vitro or in vivo in mammalian cell assays or in vitro in bacteria. No evidence of impaired fertility was observed in a study performed in male and female rats at oral dosages of up to 100 mg/kg/day.

Pregnancy

TERATOGENIC EFFECTS

Pregnancy Category C

Reproduction studies have been conducted in mice, rats and rabbits. Administration of oral doses ranging from five to ten times greater (on a mg/kg basis) than the daily recommended oral antianginal therapeutic dose has resulted in embryo and fetal lethality. These doses, in some studies, have been reported to cause skeletal abnormalities. In the perinatal/postnatal studies there was some reduction in early individual pup weights and survival rates. There was an increased incidence of stillbirths at doses of 20 times the human oral antianginal dose or greater.

There are no well-controlled studies in pregnant women; therefore, use diltiazem in pregnant women only if the potential benefit justifies the potential risk to the fetus.

Nursing Mothers

Diltiazem is excreted in human milk. One report with oral diltiazem suggests that concentrations in breast milk may approximate serum levels. If use of diltiazem is deemed essential, an alternative method of infant feeding should be instituted.

Pediatric Use

Safety and effectiveness in pediatric patients have not been established.

Geriatric Use

Clinical studies of diltiazem did not include sufficient numbers of subjects aged 65 and over to determine whether they respond differently from younger subjects. Other reported clinical experience has not identified differences in responses between the elderly and younger patients. In general, dose selection for an elderly patient should be cautious, usually starting at the low end of the dosing range, reflecting the greater frequency of decreased hepatic, renal, or cardiac function, and of concomitant disease or other drug therapy.

ATRIAL FIBRILLATION OR ATRIAL FLUTTER

In clinical studies with diltiazem hydrochloride for AF/FI, 135 of 257 patients were >65 years of age. No overall differences in safety or effectiveness were observed between these patients and younger patients, and other reported clinical experience has not identified differences in responses between the elderly and younger patients, but greater sensitivity of some older individuals cannot be ruled out.

In subgroup analysis of double-blind and open-label trials following first-dose response, 116 patients >65 years of age had a response rate of 84%. One hundred two (102) patients <65 had a response rate of 78%. In subgroup analysis following a two-dose procedure in double-blind and open-label studies, 104 patients >65 years of age and 95 patients <65 both had a 95% response rate.

PAROXYSMAL SUPRAVENTRICULAR TACHYCARDIA

Clinical studies of diltiazem hydrochloride for PSVT did not include sufficient numbers of patients aged 65 and over to determine whether they respond differently from younger patients. Other reported clinical experience has not identified differences in responses between the elderly and younger patients. In general, dose selection for an elderly patient should be cautious, usually starting at the low end of the dosing range, reflecting the greater frequency of decreased hepatic, renal, or cardiac function, and of concomitant disease or other drug therapy.

Diltiazem hydrochloride is extensively metabolized by the liver and excreted by the kidneys and in bile. The risk of toxic reactions to this drug may be greater in patients with impaired renal or hepatic function. Because elderly patients are more likely to have decreased renal function, care should be taken in dose selection, and it may be useful to monitor renal function. As with all drugs, care should be exercised when treating patients with multiple medications. (See PRECAUTIONS, General and Drug Interactions.)

ADVERSE REACTIONS

The following adverse reaction rates are based on the use of diltiazem hydrochloride injection in over 400 domestic clinical trial patients with atrial fibrillation/flutter or PSVT under double-blind or open-label conditions. Worldwide experience in over 1300 patients was similar.

Adverse events reported in controlled and uncontrolled clinical trials were generally mild and transient. Hypotension was the most commonly reported adverse event during clinical trials. Asymptomatic hypotension occurred in 4.3% of patients. Symptomatic hypotension occurred in 3.2% of patients. When treatment for hypotension was required, it generally consisted of administration of saline or placing the patient in the Trendelenburg position. Other events reported in at least 1% of the diltiazem-treated patients were injection site reactions (e.g., itching, burning) - 3.9%, vasodilation (flushing) - 1.7%, and arrhythmia (junctional rhythm or isorhythmic dissociation) - 1%.

In addition, the following events were reported infrequently (less than 1%):

Cardiovascular

Asystole, atrial flutter, AV block first degree, AV block second degree, bradycardia, chest pain, congestive heart failure, sinus pause, sinus node dysfunction, syncope, ventricular arrhythmia, ventricular fibrillation, ventricular tachycardia.

Dermatologic

Pruritus, sweating.

Gastrointestinal

Constipation, elevated SGOT or alkaline phosphatase, nausea, vomiting.

Nervous System

Dizziness, paresthesia.

Other

Amblyopia, asthenia, dry mouth, dyspnea, edema, headache, hyperuricemia. Although not observed in clinical trials with diltiazem hydrochloride injection, the following events associated with oral diltiazem may occur.

CARDIOVASCULAR

AV block (third degree), bundle branch block, ECG abnormality, palpitations, syncope, tachycardia, ventricular extrasystoles.

DERMATOLOGIC

Alopecia, erythema multiforme (including Stevens-Johnson syndrome, toxic epidermal necrolysis), exfoliative dermatitis, leukocytoclastic vasculitis, petechiae, photosensitivity, purpura, rash, urticaria.

GASTROINTESTINAL

Anorexia, diarrhea, dysgeusia, dyspepsia, mild elevations of SGPT and LDH, thirst, weight increase.

NERVOUS SYSTEM

Abnormal dreams, amnesia, depression, extrapyramidal symptoms, gait abnormality, hallucinations, insomnia, nervousness, personality change, somnolence, tremor.

OTHER

Allergic reactions, angioedema (including facial or periorbital edema), CPK elevation, epistaxis, eye irritation, gingival hyperplasia, hemolytic anemia, hyperglycemia, impotence, increased bleeding time, leukopenia, muscle cramps, myopathy, nasal congestion, nocturia, osteoarticular pain, polyuria, retinopathy, sexual difficulties, thrombocytopenia, tinnitus.

Events such as myocardial infarction have been observed which are not readily distinguishable from the natural history of the disease for the patient.

OVERDOSAGE

Overdosage experience is limited. In the event of overdosage or an exaggerated response, appropriate supportive measures should be employed. The following measures may be considered:

Bradycardia

Administer atropine (0.6 to 1 mg). If there is no response to vagal blockade administer isoproterenol cautiously.

High-Degree AV Block

Treat as for bradycardia above. Fixed high-degree AV block should be treated with cardiac pacing.

Cardiac Failure

Administer inotropic agents (isoproterenol, dopamine, or dobutamine) and diuretics.

Hypotension

Vasopressors (e.g., dopamine or levarterenol bitartrate).

The effectiveness of intravenous calcium administration to reverse the pharmacological effects of diltiazem overdose has been inconsistent. In a few reported cases, overdose with calcium channel blockers associated with hypotension and bradycardia that was initially refractory to atropine became more responsive to atropine after the patients received intravenous calcium. In some cases intravenous calcium has been administered (1 g calcium chloride or 3 g calcium gluconate) over 5 minutes, and repeated every 10 to 20 minutes as necessary. Calcium gluconate has also been administered as a continuous infusion at a rate of 2 g per hour for 10 hours. Infusions of calcium for 24 hours or more may be required. Patients should be monitored for signs of hypercalcemia.

Actual treatment and dosage should depend on the severity of the clinical situation and the judgment and experience of the treating physician.

Diltiazem does not appear to be removed by peritoneal or hemodialysis. Limited data suggest that plasmapheresis or charcoal hemoperfusion may hasten diltiazem elimination following overdose.

The intravenous LD 50s in mice and rats were 60 and 38 mg/kg, respectively. The toxic dose in man is not known.

DOSAGE AND ADMINISTRATION

Direct Intravenous Single Injections (Bolus)

The initial dose of diltiazem hydrochloride injection should be 0.25 mg/kg actual body weight as a bolus administered over 2 minutes (20 mg is a reasonable dose for the average patient). If response is inadequate, a second dose may be administered after 15 minutes. The second bolus dose of diltiazem hydrochloride injection should be 0.35 mg/kg actual body weight administered over 2 minutes (25 mg is a reasonable dose for the average patient). Subsequent intravenous bolus doses should be individualized for each patient. Patients with low body weights should be dosed on a mg/kg basis. Some patients may respond to an initial dose of 0.15 mg/kg, although duration of action may be shorter. Experience with this dose is limited.

Continuous Intravenous Infusion

For continued reduction of the heart rate (up to 24 hours) in patients with atrial fibrillation or atrial flutter, an intravenous infusion of diltiazem hydrochloride injection may be administered. Immediately following bolus administration of 20 mg (0.25 mg/kg) or 25 mg (0.35 mg/kg) diltiazem hydrochloride injection and reduction of heart rate, begin an intravenous infusion of diltiazem hydrochloride. The recommended initial infusion rate of diltiazem hydrochloride is 10 mg/h. Some patients may maintain response to an initial rate of 5 mg/h. The infusion rate may be increased in 5 mg/h increments up to 15 mg/h as needed, if further reduction in heart rate is required. The infusion may be maintained for up to 24 hours.

Diltiazem shows dose-dependent, non-linear pharmacokinetics. Duration of infusion longer than 24 hours and infusion rates greater than 15 mg/h have not been studied. Therefore, infusion duration exceeding 24 hours and infusion rates exceeding 15 mg/h are not recommended.

DILUTION

To prepare diltiazem hydrochloride injection for continuous intravenous infusion, aseptically transfer the appropriate quantity (see chart) of diltiazem hydrochloride injection to the desired volume of either Normal Saline, D5W, or D5W/0.45% NaCl. Mix thoroughly. Use within 24 hours. Keep refrigerated until use.

Diluent Volume | Quantity of Diltiazem HCl Injection to Add | Final Concentration | Administration
Diluent Volume | Quantity of Diltiazem HCl Injection to Add | Final Concentration | Dose [5 mg/h may be appropriate for some patients] | Infusion Rate
100 mL | 125 mg (25 mL) Final Volume 125 mL | 1 mg/mL | 10 mg/h 15 mg/h | 10 mL/h 15 mL/h
250 mL | 250 mg (50 mL) Final Volume 300 mL | 0.83 mg/mL | 10 mg/h 15 mg/h | 12 mL/h 18 mL/h
500 mL | 250 mg (50 mL) Final Volume 550 mL | 0.45 mg/mL | 10 mg/h 15 mg/h | 22 mL/h 33 mL/h

Compatibility

Diltiazem hydrochloride injection was tested for compatibility with three commonly used intravenous fluids at a maximal concentration of 1 mg diltiazem hydrochloride per milliliter. Diltiazem hydrochloride injection was found to be physically compatible and chemically stable in the following parenteral solutions for at least 24 hours when stored in glass or polyvinylchloride (PVC) bags at controlled room temperature 15º-30°C (59°-86°F) or under refrigeration 2°-8°C (36°-46°F).

- dextrose (5%) injection
- sodium chloride (0.9%) injection
- dextrose (5%) and sodium chloride (0.45%) injection

Physical Incompatibilities

Because of potential physical incompatibilities, it is recommended that diltiazem hydrochloride not be mixed with any other drugs in the same container. If possible, it is recommended that diltiazem hydrochloride not be co-infused in the same intravenous line.

Physical incompatibilities (precipitate formation or cloudiness) were observed when diltiazem hydrochloride injection was infused in the same intravenous line with the following drugs: acetazolamide, acyclovir, aminophylline, ampicillin, ampicillin sodium/sulbactam sodium, cefamandole, cefoperazone, diazepam, furosemide, hydrocortisone sodium succinate, insulin (regular: 100 units/mL), methylprednisolone sodium succinate, mezlocillin, nafcillin, phenytoin, rifampin, and sodium bicarbonate.

Parenteral drug products should be inspected visually for particulate matter and discoloration prior to administration, whenever solution and container permit.

Transition to Further Antiarrhythmic Therapy

Transition to other antiarrhythmic agents following administration of diltiazem hydrochloride injection is generally safe. However, reference should be made to the respective agent manufacturer’s package insert for information relative to dosage and administration.

In controlled clinical trials, therapy with antiarrhythmic agents to maintain reduced heart rate in atrial fibrillation or atrial flutter or for prophylaxis of PSVT was generally started within 3 hours after bolus administration of diltiazem hydrochloride. These antiarrhythmic agents were intravenous or oral digoxin, Class 1 antiarrthythmics (e.g., quinidine, procainamide), calcium channel blockers, and oral beta-blockers.

Experience in the use of antiarrhythmic agents following maintenance infusion of diltiazem hydrochloride injection is limited. Patients should be dosed on an individual basis and reference should be made to the respective manufacturer’s package insert for information relative to dosage and administration.

HOW SUPPLIED

Diltiazem Hydrochloride Injection 5 mg/mL is available in the following:

5 mL Vial (25 mg/vial) packaged in 10s (NDC 0641-9217-10)

10 mL Vial (50 mg/vial) packaged in 10s (NDC 0641-9218-10)

25 mL Vial (125 mg/vial) packaged in 10s (NDC 0641-9219-10)

SINGLE-DOSE VIALS. DISCARD UNUSED PORTION.

This product, including the packaging components, is free of latex.

Store diltiazem hydrochloride injection under refrigeration 2º-8ºC (36º-46ºF). DO NOT FREEZE. May be stored at room temperature for up to 1 month. Destroy after 1 month at room temperature.

To report SUSPECTED ADVERSE REACTIONS, contact Hikma Pharmaceuticals USA Inc. at 1-877-845-0689, or the FDA at 1-800-FDA-1088 or www.fda.gov/medwatch.

For Product Inquiry call 1-877-845-0689.

Manufactured by:

Hikma Pharmaceuticals USA Inc.
Berkeley Heights, NJ 07922

NOVAPLUS is a registered trademark of Vizient, Inc.

NOVAPLUS®

Revised November 2020

462-741-01

PRINCIPAL DISPLAY PANEL

NDC 0641-9217-01 Rx ONLY
Diltiazem
HCl Injection
25 mg per 5 mL (5 mg/mL)
For direct IV bolus injection
And continuous IV infusion
5 mL Single Dose Vial

NDC 0641-9217-10 Rx ONLY
Diltiazem
HCl Injection
25 mg per 5 mL (5 mg/mL)
For direct Intravenous
bolus injection
and continuous
Intravenous infusion
10 X 5 mL Single Dose Vials
NOVAPLUS

PRINCIPAL DISPLAY PANEL

NDC 0641-9218-01 Rx ONLY
Diltiazem
HCl Injection
50 mg per 10 mL (5 mg/mL)
For direct IV bolus injection
and continuous IV infusion
10 mL Single Dose Vial
NOVAPLUS

NDC 0641-9218-10 Rx ONLY
Diltiazem
HCl Injection
50 mg per 10 mL (5 mg/mL)
For direct Intravenous
bolus injection
and continuous
Intravenous infusion
10 X 10 mL Single Dose Vials
NOVAPLUS

PRINCIPAL DISPLAY PANEL

NDC 0641-9219-01 Rx ONLY
Diltiazem
HCl Injection
125 mg per 25 mL (5 mg/mL)
For direct IV bolus injection
and continuous IV infusion
25 mL Single Dose Vial
NOVAPLUS

NDC 0641-9219-10 Rx ONLY
Diltiazem
HCl Injection
125 mg per 25 mL (5 mg/mL)
For direct Intravenous
bolus injection
and continuous
Intravenous infusion
10 X 25 mL Single Dose Vials
NOVAPLUS